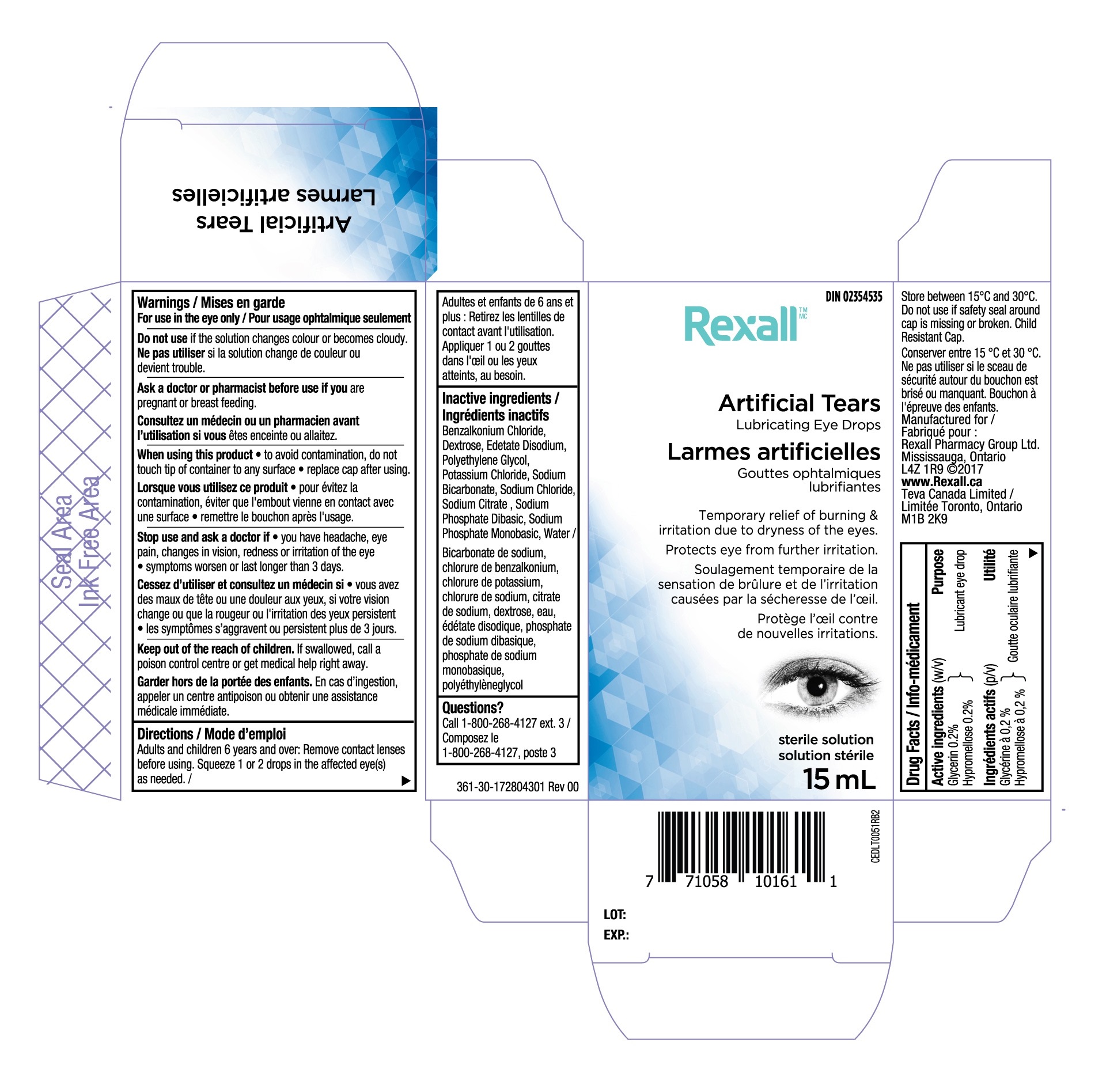 DRUG LABEL: Rexall Artificial Tears
NDC: 55651-027 | Form: SOLUTION/ DROPS
Manufacturer: KC Pharmaceuticals, Inc.
Category: otc | Type: HUMAN OTC DRUG LABEL
Date: 20251231

ACTIVE INGREDIENTS: HYPROMELLOSE, UNSPECIFIED 0.2 g/100 mL; GLYCERIN 0.2 g/100 mL
INACTIVE INGREDIENTS: BENZALKONIUM CHLORIDE; WATER; EDETATE DISODIUM; SODIUM CHLORIDE; SODIUM CITRATE; DEXTROSE; POLYETHYLENE GLYCOL, UNSPECIFIED; POTASSIUM CHLORIDE; SODIUM BICARBONATE; SODIUM PHOSPHATE, DIBASIC; SODIUM PHOSPHATE, MONOBASIC

Rexall Artificial Tears (MFR - EXPORT)